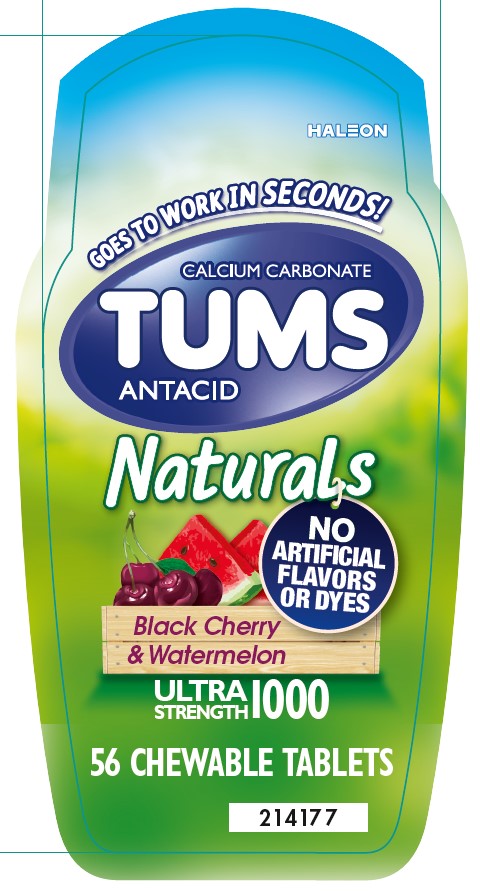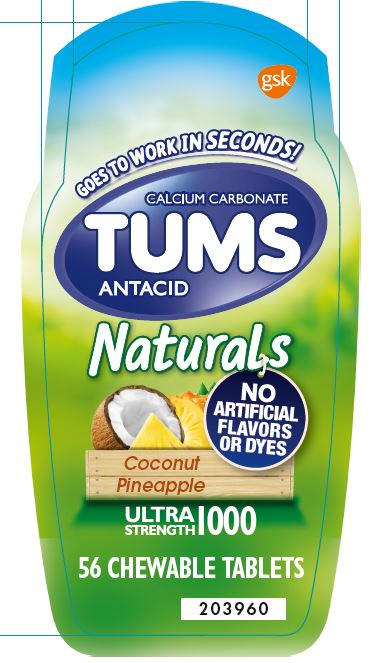 DRUG LABEL: Tums
NDC: 0135-1326 | Form: TABLET, CHEWABLE
Manufacturer: Haleon US Holdings LLC
Category: otc | Type: HUMAN OTC DRUG LABEL
Date: 20250213

ACTIVE INGREDIENTS: CALCIUM CARBONATE 1000 mg/1 1
INACTIVE INGREDIENTS: CALCIUM STEARATE; DEXTROSE, UNSPECIFIED FORM; ACACIA

Drug Facts

Active ingredient (per tablet)

Calcium carbonate 1000 mg

Purpose

Antacid

Uses

relieves

- heartburn
- acid indigestion
- sour stomach
- upset stomach associated with these symptoms

Warnings

Ask a doctor or pharmacist before use if you are

presently taking a prescription drug. Antacids may interact with certain prescription drugs.

When using this product

- do not take more than 7 tablets in 24 hours
- If pregnant do not take more than 5 tablets in 24 hours
- do not use the maximum dosage for more than 2 weeks, except under the advice and supervision of a doctor

Directions

- adults and children 12 years of age and over: chew 2-3 tablets as symptoms occur, or as directed by a doctor. Chew or crush tablets completely before swallowing.
- do not take for symptoms that persist for more than 2 weeks unless advised by a doctor

Other information

- each tablet contains: elemental calcium 400 mg
- do not store above 25°C (77°F)

Inactive ingredients (Black Cherry & Watermelon)

calcium stearate, carmine, dextrose, flavors, gum arabic

Inactive ingredients (Coconut Pineapple)

calcium stearate, dextrose, flavor, gum arabic

Questions or comments?

1-800-897-7535

Generic Section

Do not use if printed inner safety seal under cap is broken or missing.

Gluten-Free

Non-GMO

Principal Display Panel (Black Cherry & Watermelon)

GOES TO WORK IN SECONDS!

CALCIUM CARBONATE

TUMS

ANTACID

Naturals

NOARTIFICIAL FLAVORS OR DYES

Black Cherry & Watermelon

ULTRA STRENGTH 1000

56 CHEWABLE TABLETS

Principal Display Panel (Coconut Pineapple)

gsk

GOES TO WORK IN SECONDS!

CALCIUM CARBONATE

TUMS

ANTACID

NEW

Naturals

NO ARTIFICIAL FLAVORS OR DYES

Coconut Pineapple

ULTRA STRENGTH 1000

56 CHEWABLE TABLETS